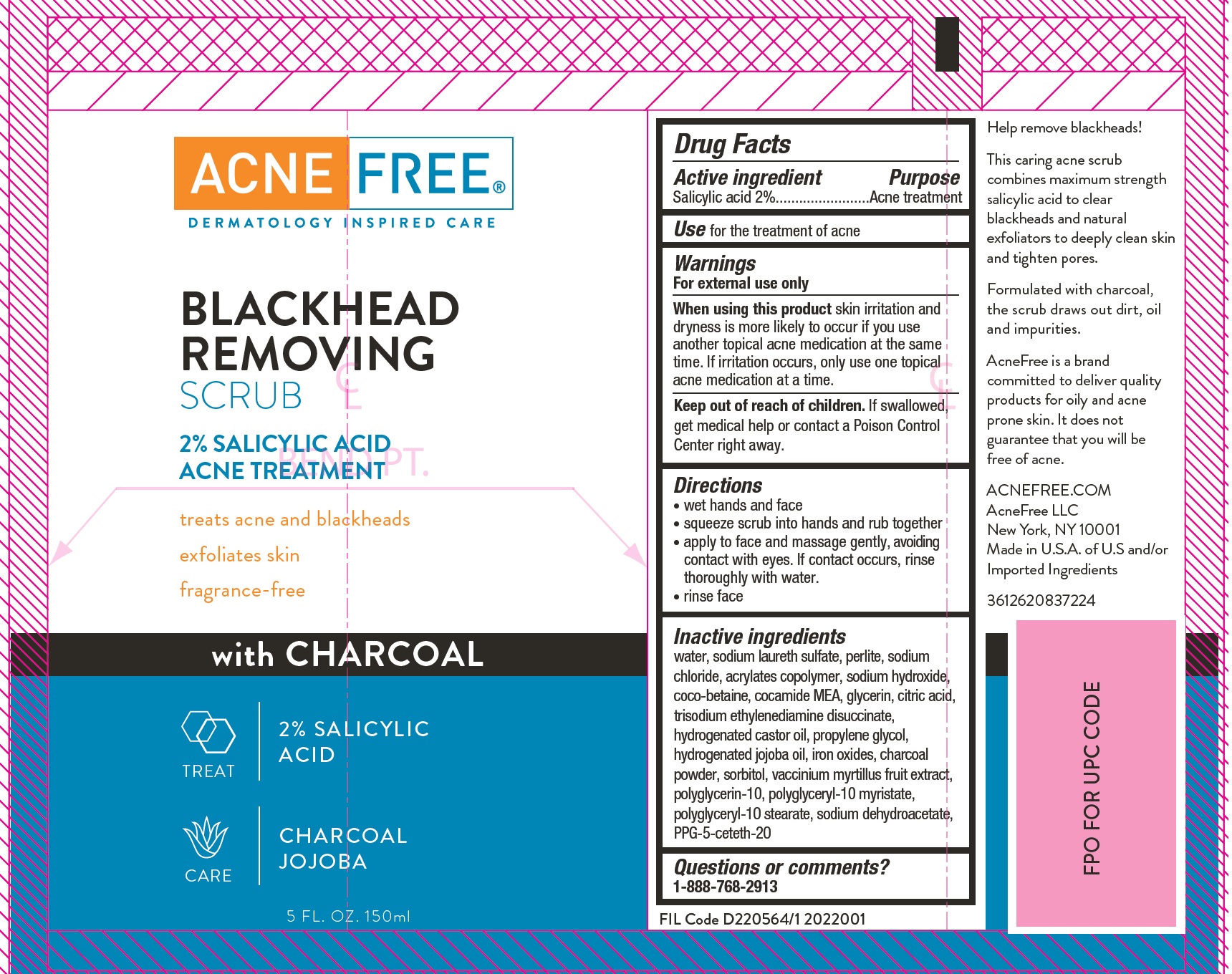 DRUG LABEL: Acne Free BLACKHEAD REMOVING SCRUB 2 Salicylic Acid with Charcoal
NDC: 80861-012 | Form: GEL
Manufacturer: AcneFree LLC
Category: otc | Type: HUMAN OTC DRUG LABEL
Date: 20250724

ACTIVE INGREDIENTS: SALICYLIC ACID 20 mg/1 mL
INACTIVE INGREDIENTS: FERRIC OXIDE RED; ACTIVATED CHARCOAL; SORBITOL; BILBERRY; WATER; SODIUM LAURETH SULFATE; PERLITE; SODIUM CHLORIDE; SODIUM HYDROXIDE; COCO-BETAINE; COCO MONOETHANOLAMIDE; GLYCERIN; CITRIC ACID MONOHYDRATE; TRISODIUM ETHYLENEDIAMINE DISUCCINATE; HYDROGENATED CASTOR OIL; PROPYLENE GLYCOL; HYDROGENATED JOJOBA OIL; POLYGLYCERIN-10; POLYGLYCERYL-10 STEARATE; SODIUM DEHYDROACETATE; PPG-5-CETETH-20

Acne Free BLACKHEAD REMOVING SCRUB 2 Salicylic Acid with Charcoal

Active ingredient

Salicylic acid 2%

Purpose

Acne treatment

Use

for the treatment of acne

Warnings

For external use only

When using this product

skin irritation and dryness is more likely to occur if you use another topical acne medication at the same time. If irritation occurs, only use one topical acne medication at a time.

Keep out of reach of children.

If swallowed, get medical help or contact a Poison Control Center right away.

Directions

• wet hands and face
• squeeze scrub into hands and rub together
• apply to face and massage gently, avoiding contact with eyes. If contact occurs, rinse thoroughly with water.
• rinse face

Inactive ingredients

water, sodium laureth sulfate, perlite, sodium chloride, acrylates copolymer, sodium hydroxide, coco-betaine, cocamide MEA, glycerin, citric acid, trisodium ethylenediamine disuccinate, hydrogenated castor oil, propylene glycol, hydrogenated jojoba oil, iron oxides, charcoal powder, sorbitol, vaccinium myrtillus fruit extract, polyglycerin-10, polyglyceryl-10 myristate, polyglyceryl-10 stearate, sodium dehydroacetate, PPG-5-ceteth-20

Questions or comments?

1-888-768-2913